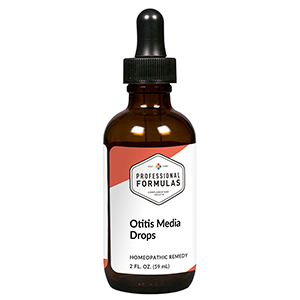 DRUG LABEL: Otitis Media Drops
NDC: 63083-2153 | Form: LIQUID
Manufacturer: Professional Complementary Health Formulas
Category: homeopathic | Type: HUMAN OTC DRUG LABEL
Date: 20190815

ACTIVE INGREDIENTS: OYSTER SHELL CALCIUM CARBONATE, CRUDE 3 [hp_X]/59 mL; PULSATILLA MONTANA WHOLE 4 [hp_X]/59 mL; ACONITUM NAPELLUS WHOLE 6 [hp_X]/59 mL; SUS SCROFA EAR 6 [hp_X]/59 mL; AMARYLLIS BELLADONNA WHOLE 12 [hp_X]/59 mL; TELLURIUM 12 [hp_X]/59 mL; FERROSOFERRIC PHOSPHATE 12 [hp_X]/59 mL; GELSEMIUM SEMPERVIRENS ROOT 30 [hp_X]/59 mL; MERCURY 30 [hp_X]/59 mL; STREPTOCOCCUS PNEUMONIAE 30 [hp_X]/59 mL; HAEMOPHILUS INFLUENZAE 60 [hp_X]/59 mL
INACTIVE INGREDIENTS: ALCOHOL; WATER

C153

ACTIVE INGREDIENTS

Calcarea carbonica 3X
Pulsatilla 4X, 12X, 30X
Aconitum napellus 6X
Ear 6X, 60X, 100X, 200X
Belladonna 12X
Tellurium metallicum 12X
Ferrum phosphoricum 12X, 30X
Gelsemium sempervirens 30X
Mercurius vivus 30X
Streptococcus pneumoniae 30X
Haemophilus influenzae 60X

QUESTIONS

Professional Formulas

PO Box 2034 Lake Oswego, OR 97035

INDICATIONS

For the temporary relief of minor earache or ringing in the ears.*

PURPOSE

*Claims based on traditional homeopathic practice, not accepted medical evidence. Not FDA evaluated.

WARNINGS

Persistent symptoms may be a sign of a serious condition. If symptoms persist or are accompanied by a fever, persistent headache, or loss of hearing, consult a doctor. Keep out of the reach of children. In case of overdose, get medical help or contact a poison control center right away. If pregnant or breastfeeding, ask a healthcare professional before use.

Keep out of the reach of children.

PREGNANCY OR BREAST FEEDING

If pregnant or breastfeeding, ask a healthcare professional before use.

DIRECTIONS

Place drops under tongue 30 minutes before/after meals. Adults and children 12 years and over: Take 10 drops up to 3 times per day. Consult a physician for use in children under 12 years of age.

OTHER INFORMATION

Tamper resistant. If seal is broken, do not use. After opening, close container tightly and store at room temperature away from heat.

INACTIVE INGREDIENTS

10% ethanol, purified water, 8% vegetable glycerin (from soy).

LABEL

Est 1985

Professional Formulas

Complementary Health

Otitis Media Drops

Homeopathic Remedy

2 FL. OZ. (59 mL)